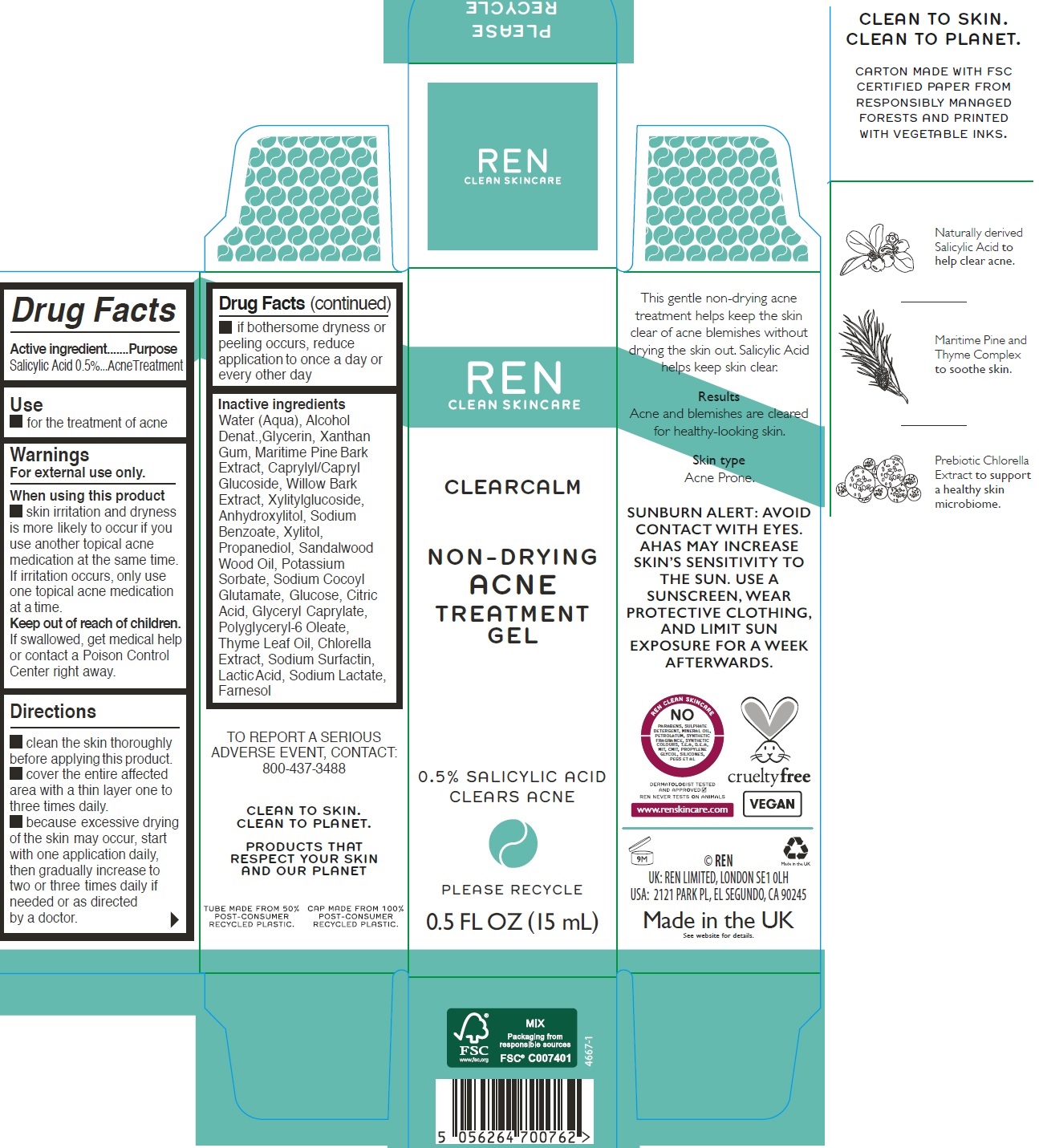 DRUG LABEL: Clearcalm Non-Drying Acne Treatment
NDC: 51417-0005 | Form: GEL
Manufacturer: Ren Ltd.
Category: otc | Type: HUMAN OTC DRUG LABEL
Date: 20231109

ACTIVE INGREDIENTS: SALICYLIC ACID 5 mg/1 mL
INACTIVE INGREDIENTS: WATER; ALCOHOL; GLYCERIN; XANTHAN GUM; CAPRYLYL/CAPRYL OLIGOGLUCOSIDE; WILLOW BARK; XYLITYLGLUCOSIDE; ANHYDROXYLITOL; SODIUM BENZOATE; XYLITOL; PROPANEDIOL; POTASSIUM SORBATE; SODIUM COCOYL GLUTAMATE; ANHYDROUS DEXTROSE; CITRIC ACID MONOHYDRATE; GLYCERYL MONOCAPRYLATE; LACTIC ACID, UNSPECIFIED FORM; SODIUM LACTATE; FARNESOL

Clearcalm Non-Drying Acne Treatment Gel

Active ingredient

Salicylic Acid 0.5%

Purpose

AcneTreatment

Use

- for the treatment of acne

Warnings

For external use only.

When using this product

skin irritation and dryness is more likely to occur if you use another topical acne medication at the same time. If irritation occurs, only use one topical acne medication at a time.

Keep out of reach of children.

If swallowed, get medical help or contact a Poison Control Center right away.

Directions

- clean the skin thoroughly before applying this product.
- cover the entire affected area with a thin layer one to three times daily.
- because excessive drying of the skin may occur, start with one application daily, then gradually increase to two or three times daily if needed or as directed by a doctor.
- if bothersome dryness or peeling occurs, reduce application to once a day or every other day

Inactive ingredients

Water (Aqua), Alcohol Denat.,Glycerin, Xanthan Gum, Maritime Pine Bark Extract, Caprylyl/Capryl Glucoside, Willow Bark Extract, Xylitylglucoside, Anhydroxylitol, Sodium Benzoate, Xylitol, Propanediol, Sandalwood Wood Oil, Potassium Sorbate, Sodium Cocoyl Glutamate, Glucose, Citric Acid, Glyceryl Caprylate, Polyglyceryl-6 Oleate, Thyme Leaf Oil, Chlorella Extract, Sodium Surfactin, Lactic Acid, Sodium Lactate, Farnesol